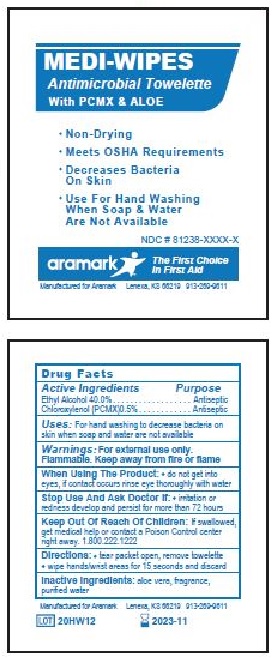 DRUG LABEL: MEDI-WIPES
NDC: 81238-5104 | Form: CLOTH
Manufacturer: Western First Aid Safety dba Aramark
Category: otc | Type: HUMAN OTC DRUG LABEL
Date: 20210521

ACTIVE INGREDIENTS: ALCOHOL 0.6 g/1.5 g; CHLOROXYLENOL 7.5 mg/1.5 g
INACTIVE INGREDIENTS: ALOE VERA LEAF; WATER

aramark MEDI-WIPES Antimicrobial Towelette

Drug Facts

Active Ingredients

Ethyl Alcohol 40.0%

Chloroxylenol (PCMX) 0.5%

Purpose

Ethyl Alcohol ................ Antiseptic

Chloroxylenol (PCMX) .... Antiseptic

Uses:

For hand washing to decrease bacteria on skin when soap and water are not available.

Warnings:

For external use only.

Flammable. Keep away from fire or flame

When Using The Product:

- do not get into eyes, if contact occurs rinse eye thoroughly with water

Stop Use And Ask Doctor If:

- if irritation or redness develop and persist for more than 72 hours

Keep Out Of Reach Of Children:

If swallowed, get medical help or contact a Poison Control center right away. 1-800-222-1222

Directions:

- tear packet open, remove towelette
- wipe hands/wrist areas for 15 seconds and discard

Inactive Ingredients:

aloe vera, fragrance, purified water

Product Label

MEDI-WIPES

Antimicrobial Towelette

With PCMX and ALOE

• Non-Drying
• Meets OSHA Requirements
• Decreases Bacteria On Skin
• Use For Hand Washing
When Soap And Water
Are Not Available

NDC# 81238-5104-1

aramark The First Choice In First Aid

Manufactured for Aramark Lenexa, KS 66219 913-269-9611

LOT

res